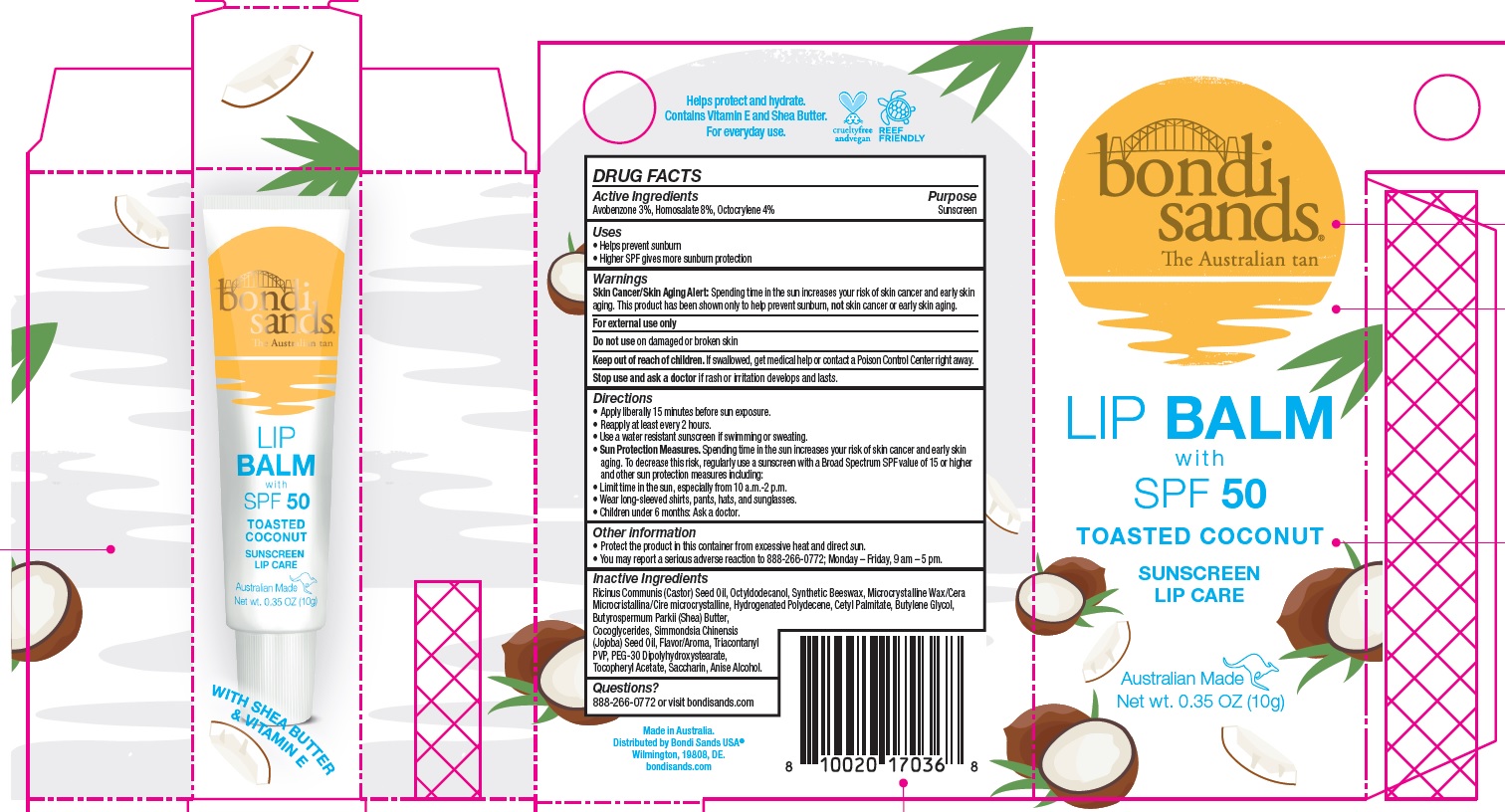 DRUG LABEL: Bondi Sands Toasted Coconut Lip Balm with SPF 50 Sunscreen
NDC: 79950-002 | Form: LIPSTICK
Manufacturer: BONDI SANDS (USA) INC.
Category: otc | Type: HUMAN OTC DRUG LABEL
Date: 20241106

ACTIVE INGREDIENTS: AVOBENZONE 30 mg/1 g; OCTOCRYLENE 40 mg/1 g; HOMOSALATE 80 mg/1 g
INACTIVE INGREDIENTS: HYDROGENATED POLYDECENE (1500 CST); CASTOR OIL; OCTYLDODECANOL; MICROCRYSTALLINE WAX; CETYL PALMITATE; BUTYLENE GLYCOL; COCO-GLYCERIDES; .ALPHA.-TOCOPHEROL ACETATE; SHEA BUTTER; JOJOBA OIL; TRICONTANYL POVIDONE; PEG-30 DIPOLYHYDROXYSTEARATE; SACCHARIN; ANISYL ALCOHOL; YELLOW WAX

Bondi Sands Toasted Coconut Lip Balm with SPF 50 Sunscreen

Active Ingredients

Avobenzone 3%, Homosalate 8%, Octocrylene 4%

Purpose

Sunscreen

Uses

- Helps prevent sunburn
- Higher SPF gives more sunburn protection

Warnings

Skin Cancer/Skin Aging Alert: Spending time in the sun increases your risk of skin cancer and early skin aging. This product has been shown only to help prevent sunburn, not skin cancer or ealy skin aging.

For external use only.

Do not use

on damaged or broken skin.

Keep out of reach of children.

If swallowed, get medical help or contact a Poison Control Center right away.

Stop use and ask a doctor

if rash or irritation develops and lasts.

Directions

- Apply liberally 15 minutes before sun exposure.
- Reapply at least every 2 hours.
- Use a water resistant sunscreen if swimming or sweating.
- Sun Protection Measures. Spending time in the sun increases your risk of skin cancer and early skin aging. To decrease this risk, regularly use a sunscreen with a Broad Spectrum SPF value of 15 or higher and other sun protection measures including:
- Limit time in the sun, especially from 10 a.m.- 2 p.m.
- Wear long-sleeved shirts, pants, hats, and sunglasses.
- Children under 6 months: Ask a doctor.

Other information

- Protect the product in this container from excessive heat and direct sun.
- You may report a serious adverse reaction to 888-266-0772; Monday – Friday, 9 am – 5 pm.

Inactive Ingredients

Ricinus Communis (Castor) Seed Oil, Octyldodecanol, Synthetic Beeswax, Microcrystalline Wax/Cera Microcristallina/Cire microcrystalline, Hydrogenated Polydecene, Cetyl Palmitate, Butylene Glycol, Butyrospermum Parkii (Shea) Butter, Cocoglycerides, Simmondsia Chinensis (Jojoba) Seed Oil, Flavor/Aroma, Triacontanyl PVP, PEG-30 Dipolyhydroxystearate, Tocopheryl Acetate, Saccharin, Anise Alcohol.

Questions?

888-266-0772 or visit bondisands.com

Company Information

Made in Australia.

Distributed by Bondi Sands USA

Wilmingon, 19808, DE.

bondisands.com

Product Packaging

bondi sands

The Australian tan

LIP BALM

with

SPF 50

TOASTED COCONUT

SUNSCREEN

LIP CARE

Australian Made

Net wt. 0.35 OZ. (10g)